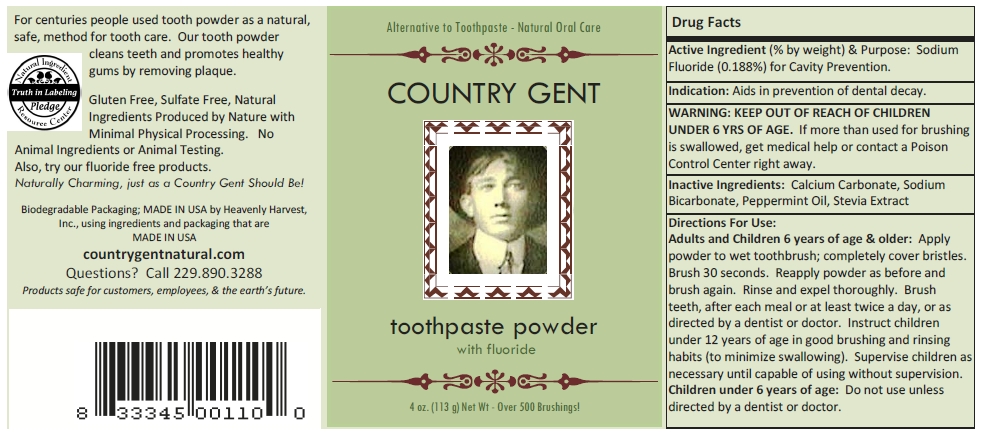 DRUG LABEL: Country Gent
NDC: 66894-0000 | Form: POWDER, DENTIFRICE
Manufacturer: Heavenly Harvest, Inc.
Category: otc | Type: HUMAN OTC DRUG LABEL
Date: 20120214

ACTIVE INGREDIENTS: SODIUM FLUORIDE 1.88 mg/1 g
INACTIVE INGREDIENTS: CALCIUM CARBONATE; SODIUM BICARBONATE; PEPPERMINT OIL; STEVIA REBAUDIANA WHOLE

Drug Facts

Active Ingredient (% by weight)

Sodium Fluoride (0.188%)

Purpose

For Cavity Prevention.

Indication

Aids in prevention of dental decay.

KEEP OUT OF REACH OF CHIL-DREN UNDER 6 YRS OF AGE.

If more than used for brushing is swallowed, get medical help or contact a Poison Control Center right away.

Inactive Ingredients

Calcium Carbonate, Sodium Bicarbonate, Peppermint Oil, Stevia Extract.

Directions For Use

Adults and Children 6 years of age & older: Apply powder to wet toothbrush; completely cover bristles. Brush 30 seconds. Reapply powder as before and brush again. Rinse and expel thoroughly. Brush teeth, after each meal or at least twice a day, or as directed by a dentist or doctor. Instruct children under 12 years of age in good brushing and rinsing habits (to minimize swallowing). Supervise children as necessary until capable of using without supervision.

Children under 6 years of age: Do not use unless directed by a dentist or doctor.

Package/Label Principal Display Panel

Country Gent

toothpaste powder

with fluoride

4 oz. (113 g) Net Wt - over 500 Brushings!

For centuries people used tooth powder as a natural,

safe, effective method for tooth care. Our tooth powder

cleans teeth and promotes healthy

gums by removing plaque.

Gluten Fee, Sulfate Free, Natura

Ingredients Produced by Nature with

Minimal Physical Processing. No

Animal Ingredients or Animal Testing.

Also, try Fluoride Free Products.

Naturally Charming, just as a Country Gent Should Be!

Biodegradable Packaging; MADE IN USA by Heavenly Harvest,

Inc., using ingredients and packaging that are

MADE IN USA

countrygentnatural.com

Questions? Call 229.890.3288

Products safe for customers, employees, & the earth's future.